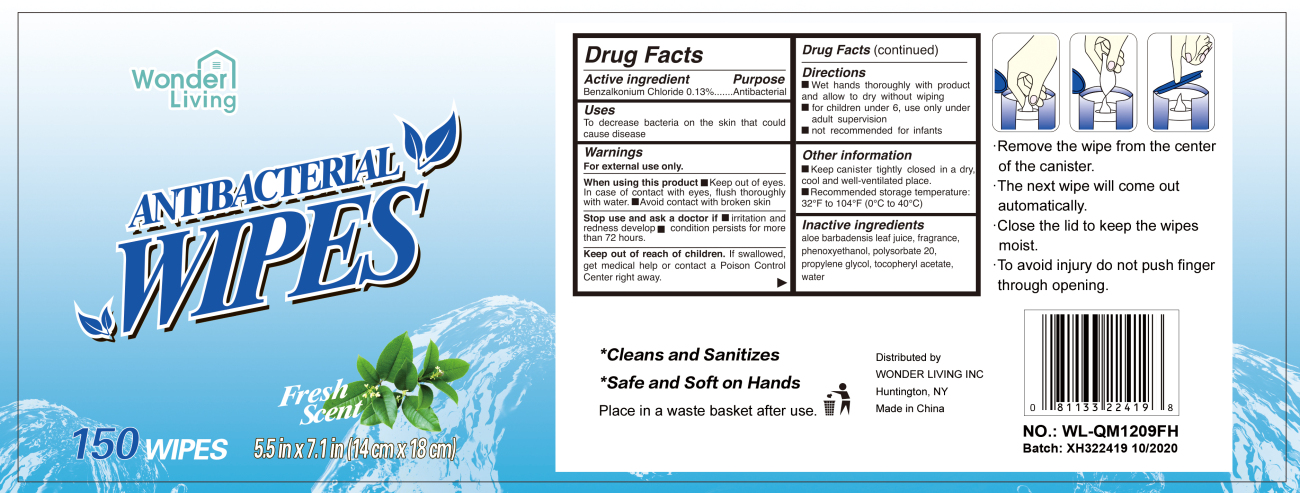 DRUG LABEL: Antibacterial wipes
NDC: 81193-001 | Form: CLOTH
Manufacturer: WONDER LIVING INC
Category: otc | Type: HUMAN OTC DRUG LABEL
Date: 20201126

ACTIVE INGREDIENTS: BENZALKONIUM CHLORIDE 0.13 g/100 g
INACTIVE INGREDIENTS: WATER; POLYSORBATE 20; PHENOXYETHANOL; PROPYLENE GLYCOL

DOSAGE AND ADMINISTRATION

Wet hands thoroughly with product and allow to dry without wiping.
For children under 6, use only under adult supervision.
Not recommended for infants.

WARNINGS

For external use only.

INACTIVE INGREDIENT

aloe barbadensis leaf juice, fragrance, phenoxyethanol, polysorbate 20, propylene glycol, tocopheryl acetate, water.

DO NOT USE

- in children less than 2 months of age
- on open skin wounds

When using this product keep out of eyes, ears, and mouth. In case of contact with eyes, rinse eyes thoroughly with water.
Stop use and ask a doctor if irritation or rash occurs. These may be signs of a serious condition.
Keep out of reach of children. If swallowed, get medical help or contact a Poison Control Center right away.

Keep out of reach of children. If swallowed, get medical help or contact a Poison Control Center right away.

ACTIVE INGREDIENT

Benzalkonium Chloride 0.13% w/w. Purpose: Antiseptic

PURPOSE

Antiseptic

INDICATIONS AND USAGE

Decreases bacteria and germs on the skin that could cause disease.

PACKAGE LABEL

150PCS DNC: 81193-001-01